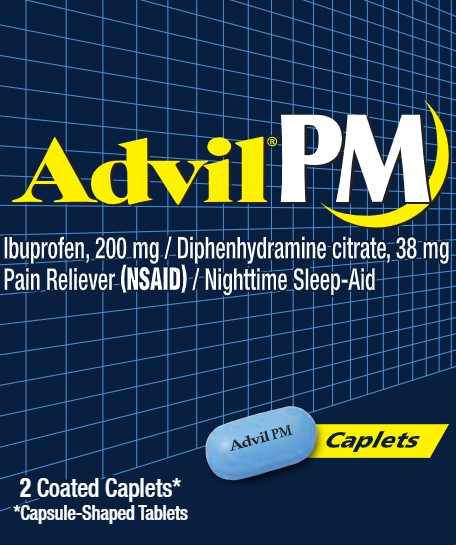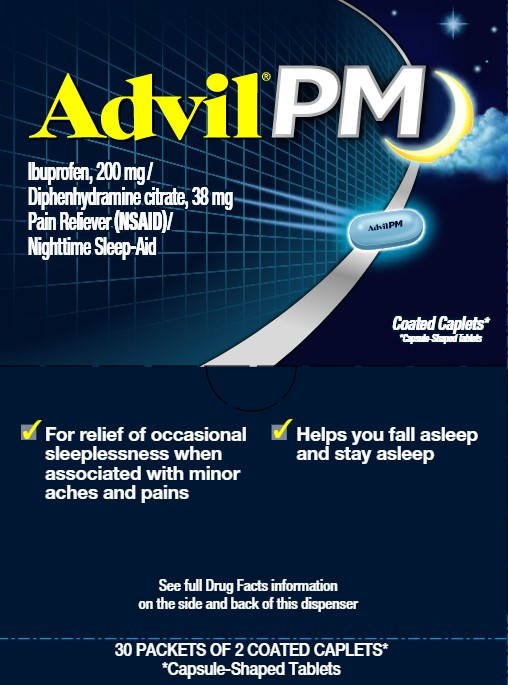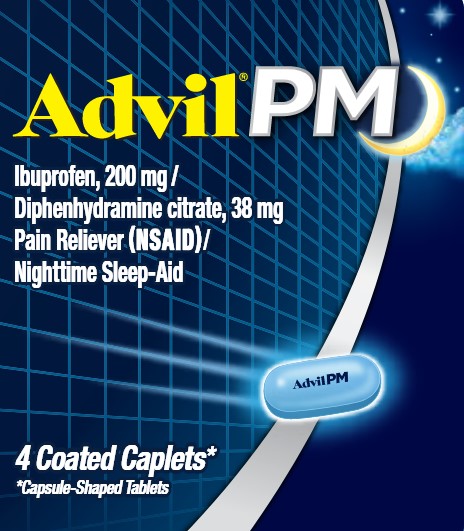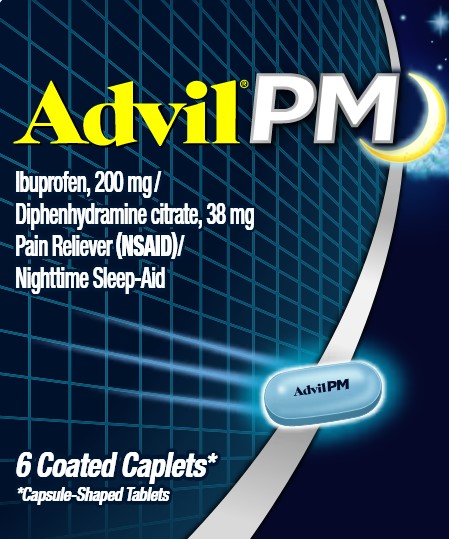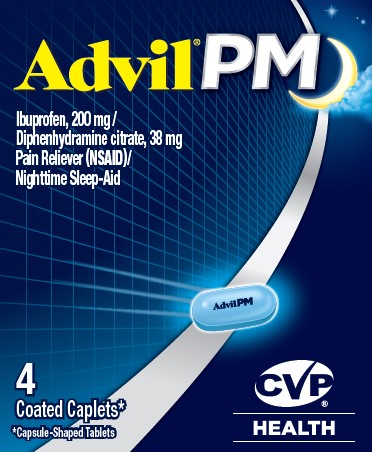 DRUG LABEL: ADVIL PM- diphenhydramine citrate and ibuprofen tablet, coated
NDC: 29485-7088 | Form: TABLET, COATED
Manufacturer: Lil Drug Store Products, Inc
Category: otc | Type: HUMAN OTC DRUG LABEL
Date: 20241230

ACTIVE INGREDIENTS: DIPHENHYDRAMINE CITRATE 38 mg/1 1; IBUPROFEN 200 mg/1 1
INACTIVE INGREDIENTS: SILICON DIOXIDE; CROSCARMELLOSE SODIUM; FD&C BLUE NO. 2; TITANIUM DIOXIDE; CALCIUM STEARATE; GLYCERYL DIBEHENATE; SODIUM LAURYL SULFATE; STARCH, CORN; POLYDEXTROSE; POLYETHYLENE GLYCOL, UNSPECIFIED; LACTOSE MONOHYDRATE; MICROCRYSTALLINE CELLULOSE; CARNAUBA WAX; STEARIC ACID; SODIUM STARCH GLYCOLATE TYPE A POTATO; HYPROMELLOSE, UNSPECIFIED

ADVIL PM- diphenhydramine citrate and ibuprofen tablet, coated

Drug Facts

Active Ingredient (in each tablet)

Diphenhydramine citrate 38 mg

Ibuprofen 200 mg (NSAID)*

*nonsteroidal anti-inflammatory drug

Purpose

Nighttime sleep-aid

Pain reliever

Uses

- for relief of occasional sleeplessness when associated with minor aches and pains
- helps you fall asleep and stay asleep

Warnings

Allergy alert

Ibuprofen may cause a severe allergic reaction, especially in people allergic to aspirin. Symptoms may include:

- hives
- facial swelling
- asthma (wheezing)
- shock
- skin reddening
- rash
- blisters

If an allergic reaction occurs, stop use and seek medical help right away.

Stomach bleeding warning:

This product contains an NSAID, which may cause severe stomach bleeding. The chance is higher if you

- are age 60 or older
- have had stomach ulcers or bleeding problems
- take a blood thinning (anticoagulant) or steroid drug
- take other drugs containing prescription or nonprescription NSAIDs [aspirin, ibuprofen, naproxen, or others]
- have 3 or more alcoholic drinks every day while using this product
- take more or for a longer time than directed

Heart attack and stroke warning:

NSAIDs, except aspirin, increase the risk of heart attack, heart failure, and stroke. These can be fatal. The risk is higher if you use more than directed or for longer than directed.

Do not use

- if you have ever had an allergic reaction to any other pain reliever/fever reducer
- unless you have time for a full night's sleep
- in children under 12 years of age
- right before or after heart surgery
- with any other product containing diphenhydramine, even one used on skin
- if you have sleeplessness without pain

Ask a doctor before use if

- stomach bleeding warning applies to you
- you have problems or serious side effects from taking pain relievers or fever reducers
- you have a history of stomach problems, such as heartburn
- you have high blood pressure, heart disease, liver cirrhosis, kidney disease, asthma, or had a stroke
- you are taking a diuretic
- you have a breathing problem such as emphysema or chronic bronchitis
- you have glaucoma
- you have trouble urinating due to an enlarged prostate gland

Ask a doctor or pharmacist before use if you are

- taking sedatives or tranquilizers, or any other sleep-aid
- under a doctor's care for any continuing medical illness
- taking any other antihistamines
- taking aspirin for heart attack or stroke, because ibuprofen may decrease this benefit of aspirin
- taking any other drug

When using this product

- drowsiness will occur
- avoid alcoholic drinks
- do not drive a motor vehicle or operate machinery
- take with food or milk if stomach upset occurs

Stop use and ask a doctor if

- you experience any of the following signs of stomach bleeding:

- feel faint
- vomit blood
- have bloody or black stools
- have stomach pain that does not get better

- you have symptoms of heart problems or stroke:

- chest pain
- trouble breathing
- weakness in one part or side of body
- slurred speech
- leg swelling

- pain gets worse or lasts more than 10 days
- sleeplessness persists continuously for more than 2 weeks. Insomnia may be a symptom of a serious underlying medical illness.
- redness or swelling is present in the painful area
- any new symptoms appear

If pregnant or breast-feeding,

ask a health professional before use. It is especially important not to use ibuprofen at 20 weeks or later in pregnancy unless definitely directed to do so by a doctor because it may cause problems in the unborn child or complications during delivery.

Keep out of reach of children.

In case of overdose, get medical help or contact a Poison Control Center right away.

Directions

- do not take more than directed
- adults and children 12 years and over: take 2 caplets at bedtime
- do not take more than 2 caplets in 24 hours

Other Information

- read all warnings and directions before use. Keep carton.
- store at 20-25°C (68-77°F)
- avoid excessive heat above 40°C (104°F)

Inactive Ingredients

calcium stearate, carnauba wax, colloidal silicon dioxide, corn starch, croscarmellose sodium, FD&C blue no. 2 aluminum lake, glyceryl dibehenate, hypromellose, lactose monohydrate, microcrystalline cellulose, pharmaceutical ink, polydextrose, polyethylene glycol, pregelatinized starch, sodium lauryl sulfate, sodium starch glycolate, stearic acid, titanium dioxide

QUESTIONS OR COMMENTS?

Call weekdays 9 AM to 5 PM EST at 1-800-88-ADVIL

PRINCIPAL DISPLAY PANEL

Advil PM

Ibuprofen, 200 mg /
Diphenhydramine citrate, 38 mg
Pain Reliever (NSAID)/
Nighttime Sleep-Aid

2 Coated Caplets*

* Capsule-Shaped Tablets

PRINCIPAL DISPLAY PANEL

Advil PM

Ibuprofen, 200 mg /
Diphenhydramine citrate, 38 mg
Pain Reliever (NSAID)/
Nighttime Sleep-Aid

4 Coated Caplets*

* Capsule-Shaped Tablets

PRINCIPAL DISPLAY PANEL

Advil PM

Ibuprofen, 200 mg /
Diphenhydramine citrate, 38 mg
Pain Reliever (NSAID)/
Nighttime Sleep-Aid

6 Coated Caplets*

* Capsule-Shaped Tablets

PRINCIPAL DISPLAY PANEL

Advil PM

Ibuprofen, 200 mg /
Diphenhydramine citrate, 38 mg
Pain Reliever (NSAID)/
Nighttime Sleep-Aid

Coated Caplets*

* Capsule-Shaped Tablets

- For relief of occasional sleeplessness when associated with minor aches and pains
- Helps you fall asleep and stay asleep

See full Drug Facts information

on the side and back of this dispenser

30 PACKETS OF 2 COATED CAPLETS*

*Capsule-Shaped Tablets

CVP 4 Count Carton

Advil PM

Ibuprofen, 200 mg /
Diphenhydramine citrate, 38 mg
Pain Reliever (NSAID)/
Nighttime Sleep-Aid

4 Coated Caplets*

* Capsule-Shaped Tablets

CVP

HEALTH